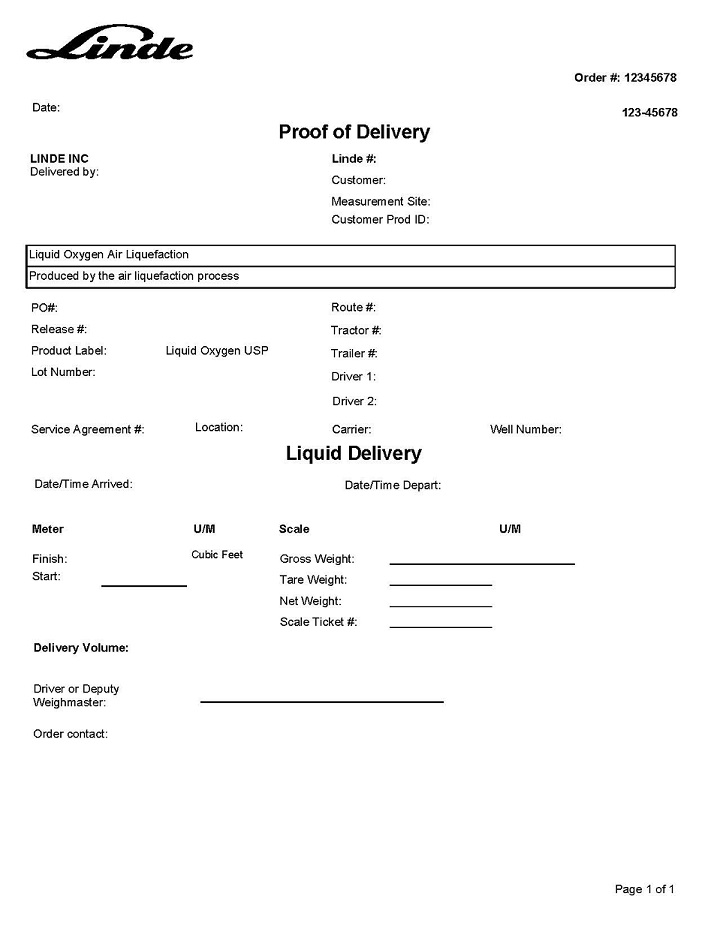 DRUG LABEL: Oxygen
NDC: 59578-721 | Form: GAS
Manufacturer: Linde Inc.
Category: prescription | Type: HUMAN PRESCRIPTION DRUG LABEL
Date: 20251230

ACTIVE INGREDIENTS: OXYGEN 990 mL/1 L

Liquid Oxygen USP